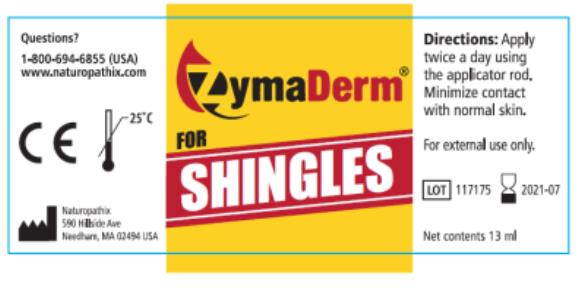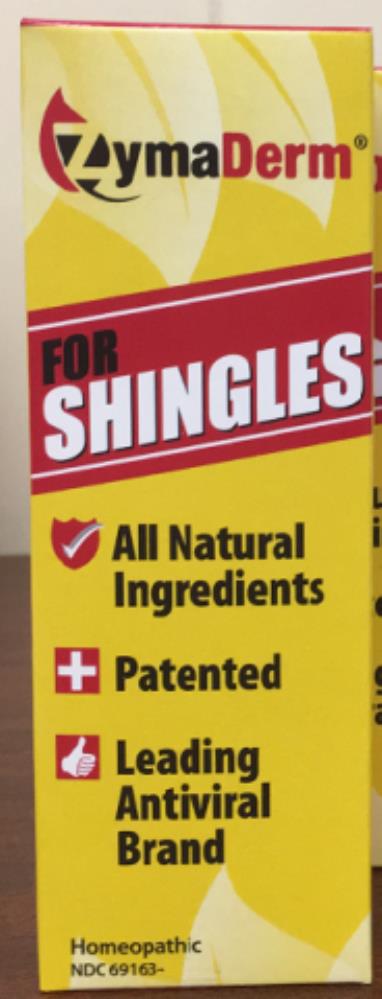 DRUG LABEL: ZymaDerm for Shingles
NDC: 69163-4137 | Form: LIQUID
Manufacturer: Naturopathix, Inc.
Category: homeopathic | Type: HUMAN OTC DRUG LABEL
Date: 20210115

ACTIVE INGREDIENTS: MELISSA OFFICINALIS 3 [hp_X]/13 mL; SILVER NITRATE 5 [hp_X]/13 mL; ECHINACEA ANGUSTIFOLIA 5 [hp_X]/13 mL; FUCUS VESICULOSUS 7 [hp_X]/13 mL
INACTIVE INGREDIENTS: JOJOBA OIL; CANOLA OIL; PEPPERMINT OIL; WEST INDIAN LEMONGRASS OIL

ZymaDerm for Shingles New

ZymaDerm®

for

Shingles

Purpose:

Topical anti-viral

Uses:

Helpful as an aid in the relief of skin symptoms caused by shingles (herpes zoster)

Directions:

- Use the applicator rod to apply a thin layer to the affected skin.
- Apply every 2 hours if possible, but at least 4 times a day.
- Begin use at the earliest sign of prodromal symptoms to help abort actual outbreaks.
- ZymaDerm™ should be applied to the blisters directly, minimizing contact with normal skin. Spills on skin should be washed with soap and water; eyes should be flushed with water in case of accidental contact; Apply enough to cover the blisters; more is not better!
- Continue use until the blisters dry up, or until the prodromal symptoms (burning, tingling, itching, pain) are gone.
- As long as you do not experience intense, persistent itchiness or discomfort, you may continue application.

Warnings:

- For External use only – ZymaDerm® contains iodine.
- ZYMADERM® IS NOT TO BE TAKEN INTERNALLY. However it may be used safely on the skin, lips, and mucosal surfaces.
- If you are pregnant, allergic to iodine, tea tree oil or any of the ingredients, consult your physician prior to use.
- Accidental contact – Eyes should be flushed with water. Ingestion: in the case of accidental ingestion, drink water and then seek medical attention. Spills on counter surfaces may be cleaned with rubbing alcohol.

Keep out of reach of children

– THIS BOTTLE IS NOT CHILD PROOF!

Purpose

3x Melissa officinalis Topical anti-viral

5x Argentum nitricum Topical antiseptic

5x Echinacea angustifolia Anti-inflammatory

7x Fucus vesiculosus Topical antiseptic

Other Ingredients:

High selenium canola oil, Essential oil of M. alternifolia, Jojoba oil, Peppermint oil, B. citriodora, and Lemongrass oil.

Distributed by Naturopathix, Inc. Boise, ID 1-800-694-6855

Net Contents ½ fl. oz.
©2019 Naturopathix, Inc. Needham MA All rights reserved. Homeopathic.
US Patent # 7,311,928

PRINCIPAL DISPLAY PANEL

ZymaDerm
FOR
SHINGLES